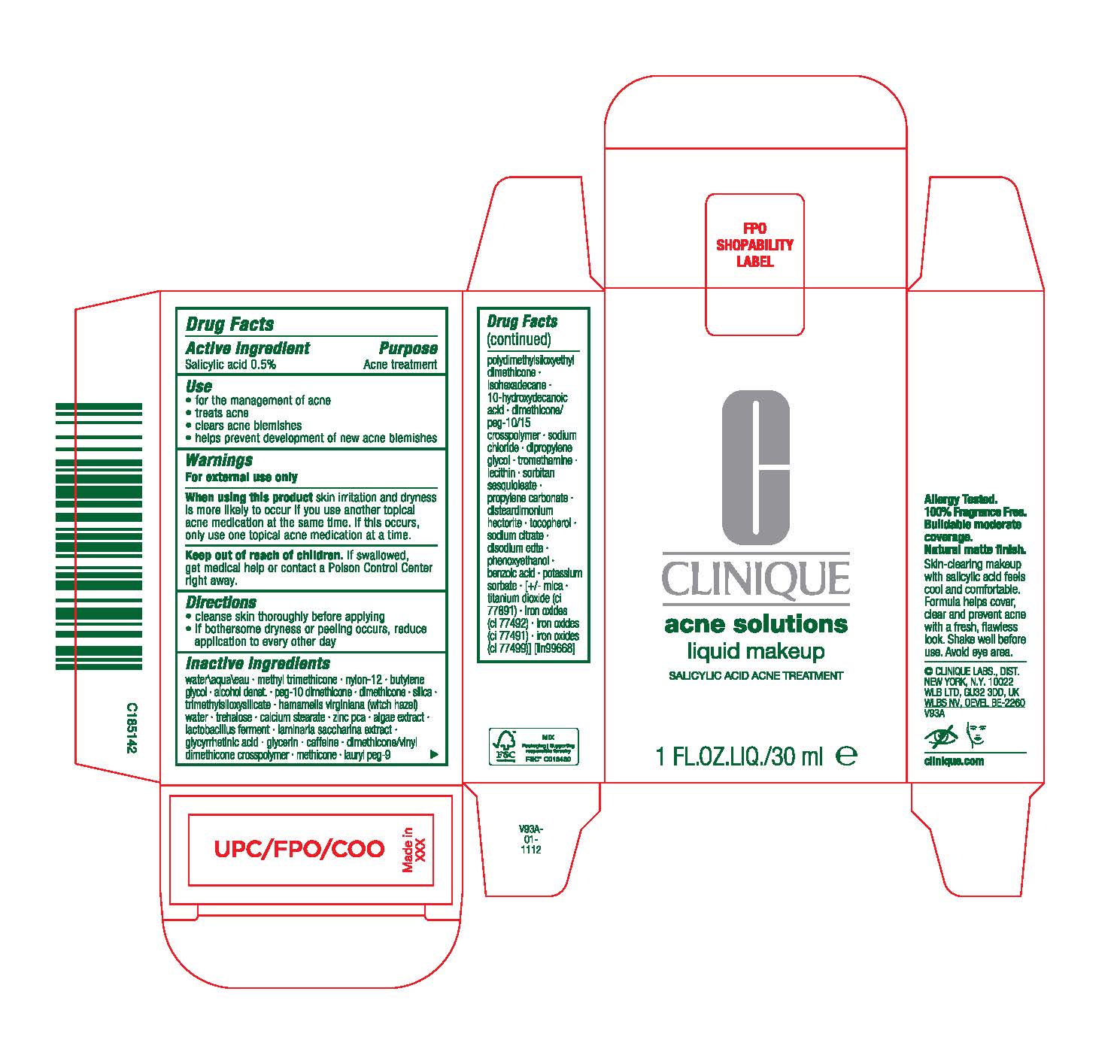 DRUG LABEL: EVEN BETTER CLINICAL ACNE SOLUTIONS
NDC: 49527-114 | Form: LIQUID
Manufacturer: CLINIQUE LABORATORIES LLC
Category: otc | Type: HUMAN OTC DRUG LABEL
Date: 20241125

ACTIVE INGREDIENTS: SALICYLIC ACID 5 mg/1 mL
INACTIVE INGREDIENTS: WATER; METHYL TRIMETHICONE; ALCOHOL; TREHALOSE; CALCIUM STEARATE; ZINC PIDOLATE; LIMOSILACTOBACILLUS REUTERI; CAFFEINE; ISOHEXADECANE; LECITHIN, SOYBEAN; DISTEARDIMONIUM HECTORITE; SACCHARINA LATISSIMA; 10-HYDROXYDECANOIC ACID; DIMETHICONE; PROPYLENE CARBONATE; DIPROPYLENE GLYCOL; EDETATE DISODIUM ANHYDROUS; POTASSIUM SORBATE; MICA; TITANIUM DIOXIDE; FERRIC OXIDE YELLOW; PHENOXYETHANOL; BENZOIC ACID; SORBITAN SESQUIOLEATE; NYLON-12; BUTYLENE GLYCOL; PEG-10 DIMETHICONE (600 CST); SILICON DIOXIDE; TRIMETHYLSILOXYSILICATE (M/Q 0.6-0.8); HAMAMELIS VIRGINIANA TOP WATER; PORPHYRIDIUM PURPUREUM; ENOXOLONE; GLYCERIN; DIMETHICONE/VINYL DIMETHICONE CROSSPOLYMER (HARD PARTICLE); METHICONE (20 CST); LAURYL PEG-9 POLYDIMETHYLSILOXYETHYL DIMETHICONE; DIMETHICONE/PEG-10/15 CROSSPOLYMER; SODIUM CHLORIDE; TROMETHAMINE; TOCOPHEROL; SODIUM CITRATE; FERRIC OXIDE RED; FERROSOFERRIC OXIDE

EVEN BETTER CLINICAL ACNE SOLUTIONS

Active Ingredients

SALICYLIC ACID 0.5%

Purpose

Acne treatment

USE

for the management of acne

treats acne

clears acne blemishes

helps prevent development of new acne blemishes

Warnings

For external use only

When using this product skin irritation and dryness is more likely to occur if you use another topical acne medication at the same time. If this occurs, use only one topical acne medication at a time.

Keep out of reach of children. If swallowed, get medical help or contact a Poison Control Center right away.

Directions

cleanse skin thoroughly before applying
if bothersome dryness or peeling occurs, reduce application to every other day

Inactive ingredients

water\aqua\eau· methyl lrimethicone· nylon-12· butylene glycol · aloohol denat.· peg-10 dimelhicme ·dimelhioone· silica· trimelhylsiloxysilicale · hamamelis virginiana(witchhazel) water · trnhalose·calcium stearate · zinc r:ca · algae extract · lactobacillusferment·laminaria saccharina extract·glycyrrhetinicacid · glycerin· caffeine·dimethicone/vinyl dimethiconeCflliSilllymer· melhioone ·lauryl peg-9 polydimethylsiloxyethyl dimethicone ·isohexadecane ·10-hyoroxydecanoic acid· dimethicone/ peg-10/15 crosspolymer· sodium chloride· dipropylene glycol· tromethamine · lecithin·sorbitan sesquioleate · propylene cartrnate· disteardimonium hectonte · tocopherol· sodium citrate· diso:Jiumedta· phenoxyethanol · oonzoicacid· potassium sorbate · [+/-mica· titaniumdioxide(ci 77891) · ironoxides(ci 77492) · iron oxides (ci 77491) · iron oxides (ci 77499)] [iln99668]

PRINCIPAL DISPLAY PANEL

CLINIQUE
acne solutions
liquid makeup
SALICYLIC ACID ACNE TREATMENT

1 FL.OZ.LIQ./30ml